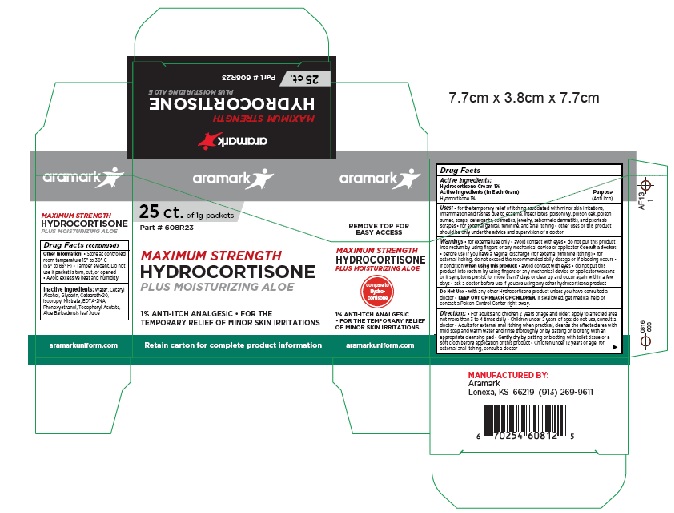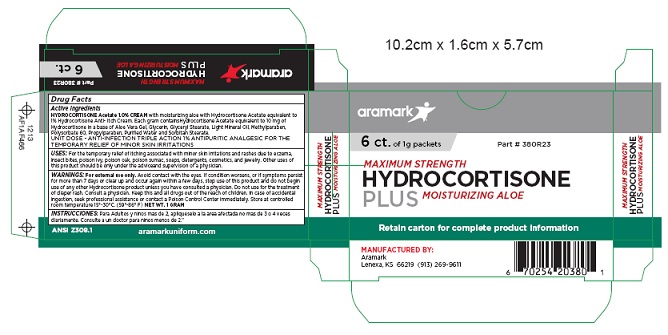 DRUG LABEL: Maximum Strength Hydrocortisone Plus Moisturizing Aloe
NDC: 81238-4608 | Form: CREAM
Manufacturer: Western First Aid Safety dba Aramark
Category: otc | Type: HUMAN OTC DRUG LABEL
Date: 20210521

ACTIVE INGREDIENTS: HYDROCORTISONE 10 mg/1 g
INACTIVE INGREDIENTS: WATER; CETOSTEARYL ALCOHOL; GLYCERIN; POLYOXYL 20 CETOSTEARYL ETHER; ISOPROPYL MYRISTATE; EDETATE DISODIUM; PHENOXYETHANOL; .ALPHA.-TOCOPHEROL ACETATE, D-; ALOE VERA LEAF

aramark Maximum Strength Hydrocortisone Plus Moisturizing Aloe

Drug Facts

Active Ingredients:
Hydrocortisone Cream 1%
Active Ingredients (In Each Gram)

Purpose
Hydrcortisone 1% ...... Anti Itch

INDICATIONS AND USAGE

Uses: • for the temporary relief of itching associated with minor skin irritations,
inflammation and rashes due to eczema, insect bites, poison ivy, poison oak, poison
sumac, soaps, detergents, cosmetics, jewelry, seborrheic dermatitis, and psoriasis
scrapes • for external genital, feminine, and anal itching • other uses of this product
should be only under the advice and supervision of a doctor

WARNINGS

Warnings • for external use only • avoid contact with eyes • do not put this product
into rectum by using fingers or any mechanical device or applicator Consult a doctor:
• before use if you have a vaginal discharge (for external feminine itching) • for
external itching, do not exceed the recommended daily dosage or if bleeding occurs •
if condition When using this product: • avoid contact with eyes • do not put this
product into rectum by using fingers or any mechanical device or applicator worsens
or if symptoms persist for more than 7 days or clear up and occur again within a few
days • ask a doctor before use if you are using any other hydrocortisone product

Do Not Use • with any other Hydrocortisone product unless you have consulted a
doctor

• KEEP OUT OF REACH OF CHILDREN. If swallowed, get medical help or
contact a Poison Control Center right away.

DOSAGE AND ADMINISTRATION

Directions: • For adults and children 2 years of age and older: apply to affected area
not more than 3 to 4 times daily • Children under 2 years of age: do not use, consult a
doctor • Adults for external anal itching when practical, cleanse the affected area with
mild soap and warm water and rinse thoroughly or by patting or blotting with an
appropriate cleansing pad • Gently dry by patting or blotting with toilet tissue or a
soft cloth before application of this product • Children under 12 years of age: for
external anal itching, consult a doctor

Other Information: • Store at controlled
room temperature 15° to 30° C
(59° to 86° F) • Tamper evident. Do not
use if packet is torn, cut, or opened
• Avoid excessive heat and humidity

Inactive Ingredients: Water, Cetaryl
Alcohol, Glycerin, Ceteareth-20,
Isopropyl Mistrate, EDTA-2NA,
Phenoxyethanol, Tocopheryl Acetate,
Aloe Barbadensis leaf Juice

Product Package

aramark

25 ct. of 1g packets

Part # 608R23

MAXIMUM STRENGTH
HYDROCORTISONE
PLUS MOISTURIZING ALOE

compare to
Hydrocortisone

1% ANTI-ITCH ANALGESIC • FOR THE

TEMPORARY RELIEFOF MINOR SKIN IRRITATIONS

Retain carton for complete product information

MANUFACTURED BY:
Aramark
Lenexa, KS 66219 (913) 269-9611

aramarkuniform.com

25 Count

6 Count